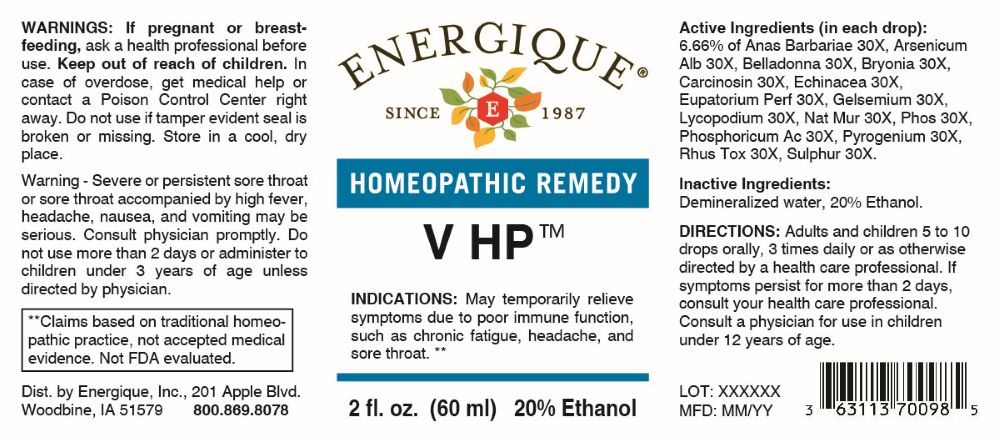 DRUG LABEL: V
NDC: 44911-0680 | Form: LIQUID
Manufacturer: Energique, Inc.
Category: homeopathic | Type: HUMAN OTC DRUG LABEL
Date: 20251204

ACTIVE INGREDIENTS: CAIRINA MOSCHATA HEART/LIVER AUTOLYSATE 30 [hp_X]/1 mL; ARSENIC TRIOXIDE 30 [hp_X]/1 mL; ATROPA BELLADONNA 30 [hp_X]/1 mL; BRYONIA ALBA ROOT 30 [hp_X]/1 mL; HUMAN BREAST TUMOR CELL 30 [hp_X]/1 mL; ECHINACEA ANGUSTIFOLIA WHOLE 30 [hp_X]/1 mL; EUPATORIUM PERFOLIATUM FLOWERING TOP 30 [hp_X]/1 mL; GELSEMIUM SEMPERVIRENS ROOT 30 [hp_X]/1 mL; LYCOPODIUM CLAVATUM SPORE 30 [hp_X]/1 mL; SODIUM CHLORIDE 30 [hp_X]/1 mL; PHOSPHORIC ACID 30 [hp_X]/1 mL; PHOSPHORUS 30 [hp_X]/1 mL; RANCID BEEF 30 [hp_X]/1 mL; TOXICODENDRON PUBESCENS LEAF 30 [hp_X]/1 mL; SULFUR 30 [hp_X]/1 mL
INACTIVE INGREDIENTS: WATER; ALCOHOL

DRUG FACTS:

ACTIVE INGREDIENTS:

(in each drop): 6.66% of Anas Barbariae 30X, Arsenicum Album 30X, Belladonna 30X, Bryonia 30X, Carcinosin 30X, Echinacea 30X, Eupatorium Perfoliatum 30X, Gelsemium Sempervirens 30X, Lycopodium Clavatum 30X, Natrum Muriaticum 30X, Phosphoricum Acidum 30X, Phosphorus 30X, Pyrogenium 30X, Rhus Tox 30X, Sulphur 30X.

PURPOSE:

May temporarily relieve symptoms due to poor immune function, such as chronic fatigue, headache, and sore throat.**

**Claims based on traditional homeopathic practice, not accepted medical evidence Not FDA evaluated.

WARNINGS:

If pregnant or breast-feeding, ask a health professional before use.

Keep out of reach of children. In case of overdose, get medical help or contact a Poison Control Center right away.

Do not use if tamper evident seal is broken or missing.

Store in a cool, dry place.

Severe or persistent sore throat or sore throat accompanied by a high fever, headache, nausea, and vomiting may be serious. Consult physician promptly. Do not use more than 2 days or administer to children under 3 years of age unless directed by physician.

KEEP OUT OF REACH OF CHILDREN:

In case of overdose, get medical help or contact a Poison Control Center right away.

DIRECTIONS:

Adults and children 5 to 10 drops orally, 3 times daily or as otherwise directed by a health care professional.

If symptoms persist for more than 2 days, consult your health care professional.

Consult a physician for use in children under 12 years of age.

INDICATIONS:

May temporarily relieve symptoms due to poor immune function, such as chronic fatigue, headache, and sore throat.**

**Claims based on traditional homeopathic practice, not accepted medical evidence Not FDA evaluated.

INACTIVE INGREDIENTS:

Demineralized water, 20% Ethanol.

QUESTIONS:

Dist. By: Energique Inc.

201 Apple Blvd.

Woodbine, IA 51579

800.869.8078

PACKAGE LABEL DISPLAY:

ENERGIQUE

SINCE 1987

HOMEOPATHIC REMEDY

V HP

2 fl. oz. (60 ml)